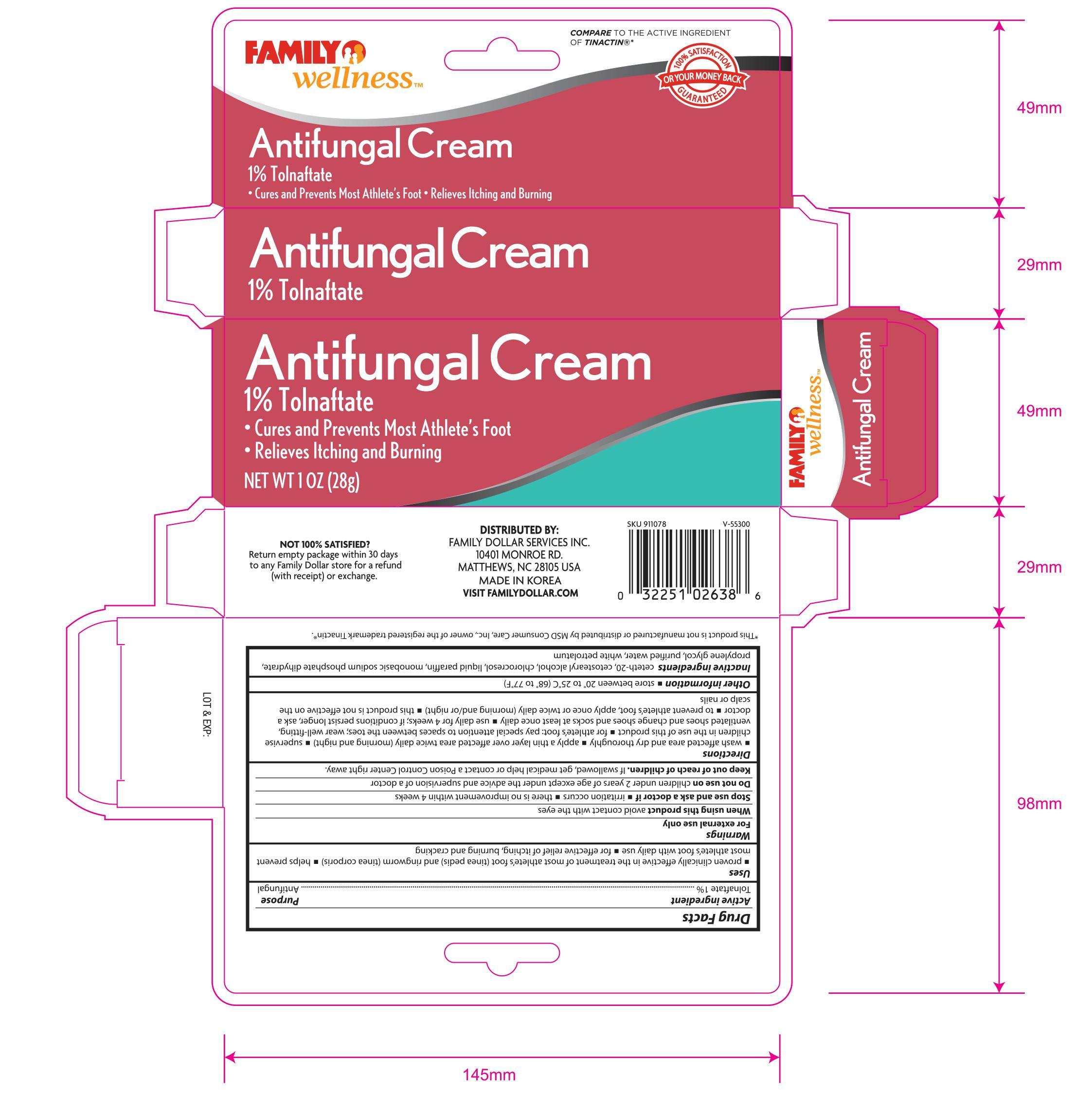 DRUG LABEL: Family Wellness Antifungal
NDC: 55319-638 | Form: CREAM
Manufacturer: Family Dollar
Category: otc | Type: HUMAN OTC DRUG LABEL
Date: 20140121

ACTIVE INGREDIENTS: TOLNAFTATE 1 g/100 g
INACTIVE INGREDIENTS: CETETH-20; CETOSTEARYL ALCOHOL; CHLOROCRESOL; PARAFFIN; MAGNESIUM PHOSPHATE, MONOBASIC, DIHYDRATE; PROPYLENE GLYCOL; WATER; PETROLATUM

Active Ingredient Purpose

Tolnaftate 1%................................................ Antifungal

Uses

- proven clinically effective in the treatment of most athlete's foot (tinea pedis) and ringworm (tinea corporis)
- helps prevent most athlete's foot with daily use
- for effective relief of itching, burning, and cracking

Warnings

For external use only

When using this product avoid contact with the eyes

Stop use and ask a doctor if

- irritation occurs
- there is no improvement within 4 weeks

Do not use on children under 2 years of age except under the advice and supervision of a doctor

Keep out of reach of children. If swallowed, get medical help or contact a Poision Control Center right away.

Directions

- wash affected area and dry thoroughlyapply a thin layer over affected area twice daily (morning and night)
- supervise children in the use of this product
- for athlete's foot: pay special attention to spaces between the toes; wear well-fitting, ventilated shoes and change shoes and socks at least once daily
- use daily for 4 weeks; if conditions persist longer, ask doctor
- to prevent athlete's foot, apply once or twice daily (morning and/or night)
- this product is not effective on the scalp or nails

Other information

- store between 20°C to 25°C (68°F to 77°F)

Inactive ingredients

ceteth-20, cetostearyl alcohol, chlorocresol, liquid paraffin, monorask sodium phosphate dilhydrate, propylene glycol, purified water, white petrolatum

DOSAGE AND ADMINISTRATION

DISTRIBUTED BY:

FAMILY DOLLAR SERVICES INC.

10401 MONROE RD.

MATTHEWS, NC 28105 USA